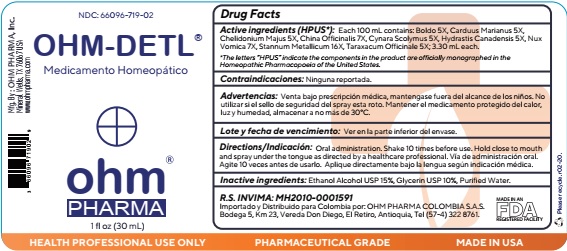 DRUG LABEL: OHM-DETL
NDC: 66096-719 | Form: SPRAY
Manufacturer: OHM PHARMA INC.
Category: homeopathic | Type: HUMAN OTC DRUG LABEL
Date: 20200218

ACTIVE INGREDIENTS: PEUMUS BOLDUS LEAF 5 [hp_X]/30 mL; MILK THISTLE 5 [hp_X]/30 mL; CHELIDONIUM MAJUS WHOLE 5 [hp_X]/30 mL; CINCHONA OFFICINALIS BARK 7 [hp_X]/30 mL; CYNARA SCOLYMUS LEAF 5 [hp_X]/30 mL; GOLDENSEAL 5 [hp_X]/30 mL; STRYCHNOS NUX-VOMICA SEED 7 [hp_X]/30 mL; TIN 16 [hp_X]/30 mL; TARAXACUM OFFICINALE 5 [hp_X]/30 mL
INACTIVE INGREDIENTS: ALCOHOL; GLYCERIN; WATER

OHM-DETL

ACTIVE INGREDIENT

Active ingredients (HPUS*): Each 100 mL contains: Boldo 5X, Carduus Marianus 5X,
Chelidonium Majus 5X, China Officinalis 7X, Cynara Scolymus 5X, Hydrastis Canadensis 5X, Nux
Vomica 7X, Stannum Metallicum 16X, Taraxacum Officinale 5X; 3.30 mL each.

*The letters “HPUS” indicate the components in the product are officially monographed in the
Homeopathic Pharmacopoeia of the United States.

INDICATIONS AND USAGE

Contraindicaciones: Ninguna reportada

WARNINGS

Advertencias: Venta bajo prescripción médica, mantengase fuera del alcance de los niños. No
utilizar si el sello de seguridad del spray esta roto. Mantener el medicamento protegido del calor,
luz y humedad, almacenar a no más de 30°C.

KEEP OUT OF REACH OF CHILDREN

Mantengase fuera del alcance de los niños

DOSAGE AND ADMINISTRATION

Directions/Indicación: Oral administration. Shake 10 times before use. Hold close to mouth
and spray under the tongue as directed by a healthcare professional. Vía de administración oral.
Agite 10 veces antes de usarlo. Aplique directamente bajo la lengua según indicación médica.

INACTIVE INGREDIENT

Inactive ingredients: Ethanol Alcohol USP 15%, Glycerin USP 10%, Purified Water.

OTHER SAFETY INFORMATION

Lote y fecha de vencimiento: Ver en la parte inferior del envase

QUESTIONS

R.S. INVIMA: MH2010-0001591
Importado y Distribuido para Colombia por: OHM PHARMA COLOMBIA S.A.S.
Bodega 5, Km 23, Vereda Don Diego, El Retiro, Antioquia, Tel (57-4) 322 8761.

Mfg. By : OHM PHARMA, Inc.
Mineral Wells, TX 76067 USA
www.ohmpharma.com

PACKAGE LABEL

NDC: 66096-719-02

OHM-DETL

ohm

PHARMA

1 fl oz (30 mL)

PURPOSE

Medicamento Homeopático